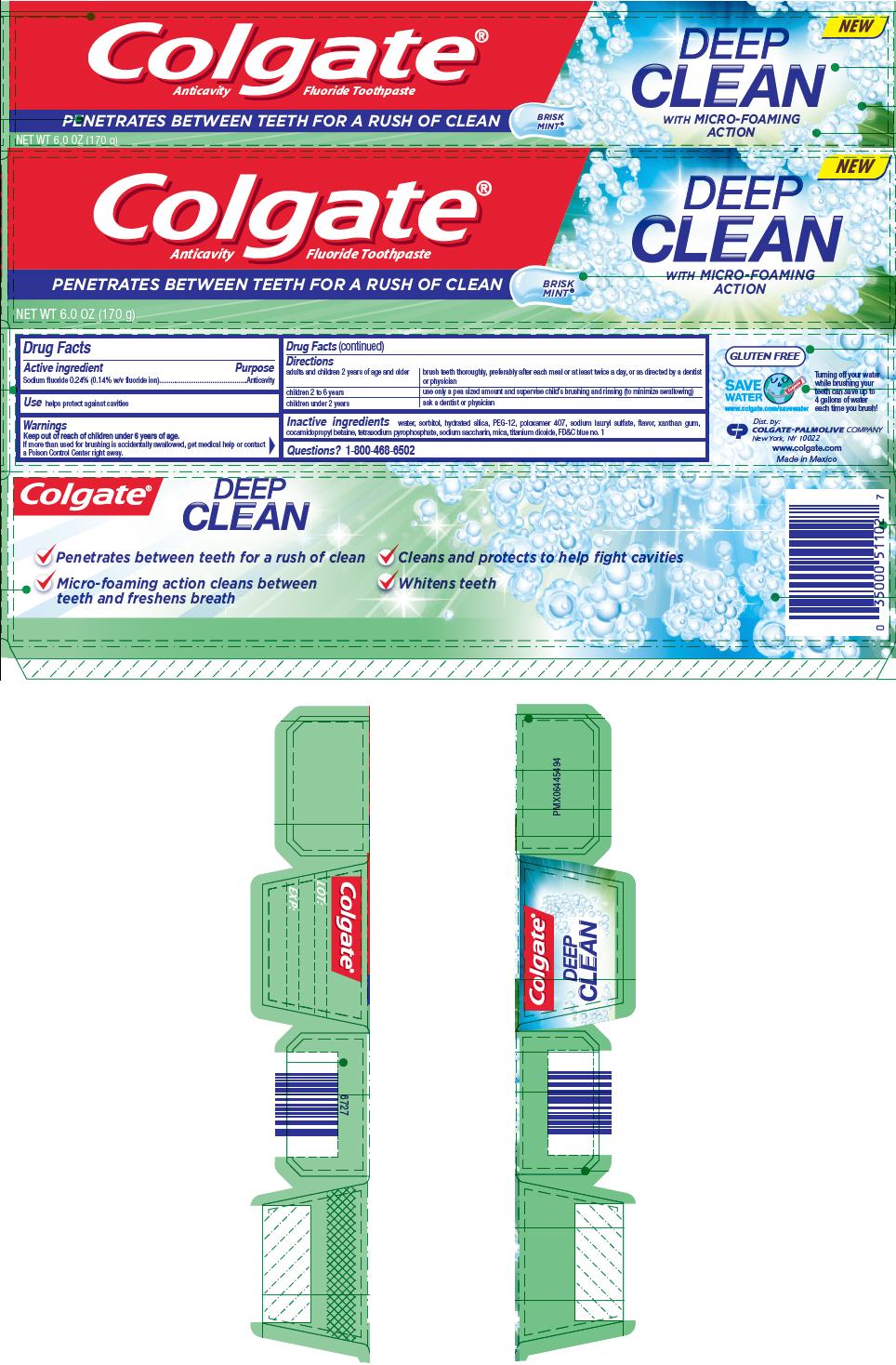 DRUG LABEL: Colgate Deep Clean Fluoride
NDC: 35000-969 | Form: GEL, DENTIFRICE
Manufacturer: Colgate-Palmolive Company
Category: otc | Type: HUMAN OTC DRUG LABEL
Date: 20191218

ACTIVE INGREDIENTS: SODIUM FLUORIDE 1.1 mg/1 g
INACTIVE INGREDIENTS: WATER 249.848 mg/1 g; SORBITOL; HYDRATED SILICA; POLYETHYLENE GLYCOL 600; POLOXAMER 407; SODIUM LAURYL SULFATE; XANTHAN GUM; COCAMIDOPROPYL BETAINE; SODIUM PYROPHOSPHATE; SACCHARIN SODIUM; MICA; TITANIUM DIOXIDE; FD&C BLUE NO. 1

Colgate® Deep Clean Fluoride Toothpaste

Drug Facts

Active ingredient

Sodium fluoride 0.24% (0.14% w/v fluoride ion)

Purpose

Anticavity

Use

helps protect against cavities

Warnings

Keep out of reach of children under 6 years of age.

If more than used for brushing is accidentally swallowed, get medical help or contact a Poison Control Center right away.

Directions

adults and children 2 years of age and older | brush teeth thoroughly, preferably after each meal or at least twice a day, or as directed by a dentist or physician
children 2 to 6 years | use only a pea sized amount and supervise child's brushing and rinsing (to minimize swallowing)
children under 2 years | ask a dentist or physician

Inactive ingredients

water, sorbitol, hydrated silica, PEG-12, poloxamer 407, sodium lauryl sulfate, flavor, xanthan gum, cocamidopropyl betaine, tetrasodium pyrophosphate, sodium saccharin, mica, titanium dioxide, FD&C blue no. 1

Questions?

1-800-468-6502

Dist. by:
COLGATE-PALMOLIVE COMPANY
New York, NY 10022

PRINCIPAL DISPLAY PANEL - 170 g Tube Carton

Colgate®
Anticavity Fluoride Toothpaste

PENETRATES BETWEEN TEETH FOR A RUSH OF CLEAN

BRISK
MINT®

NET WT 6.0 OZ (170 g)

NEW

DEEP
CLEAN
WITH MICRO-FOAMING
ACTION